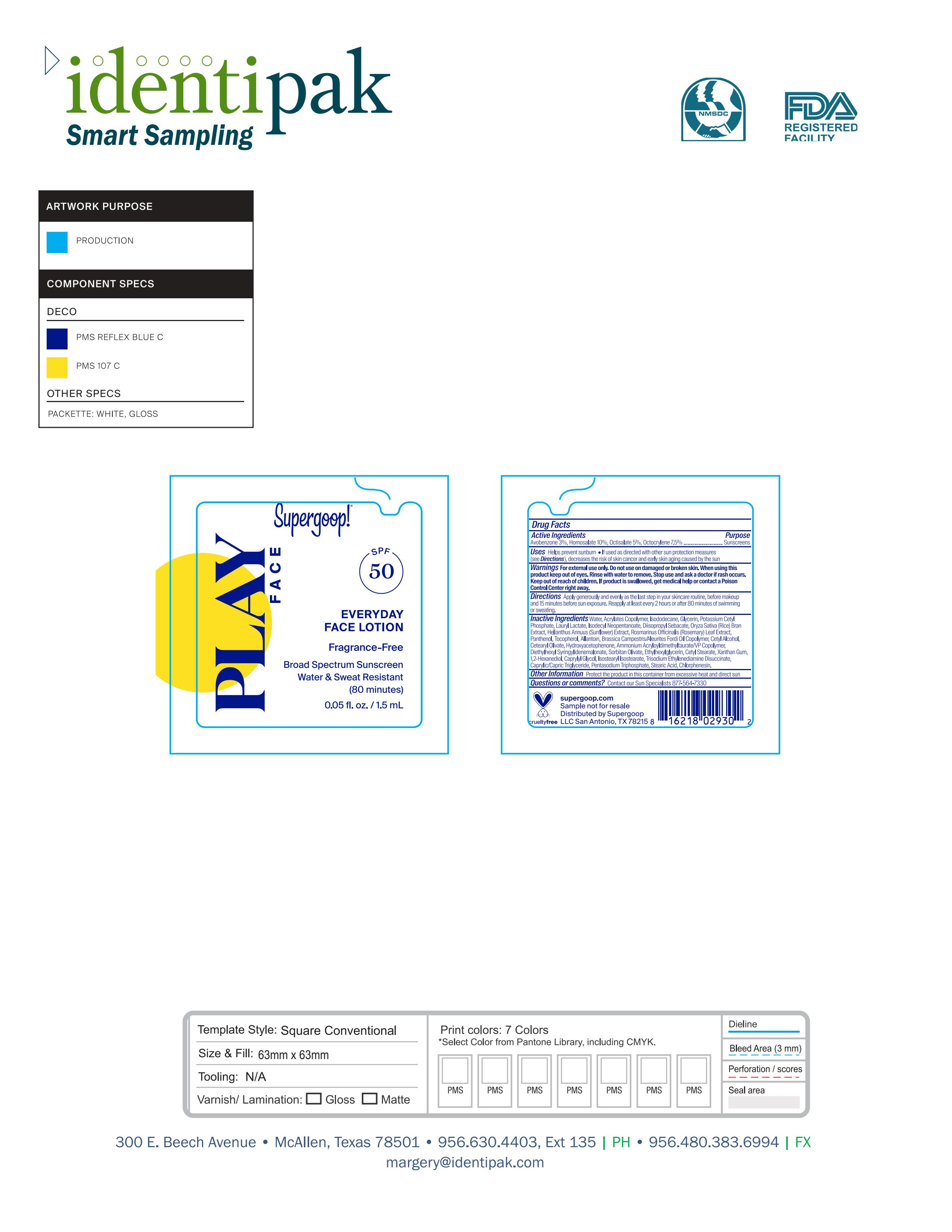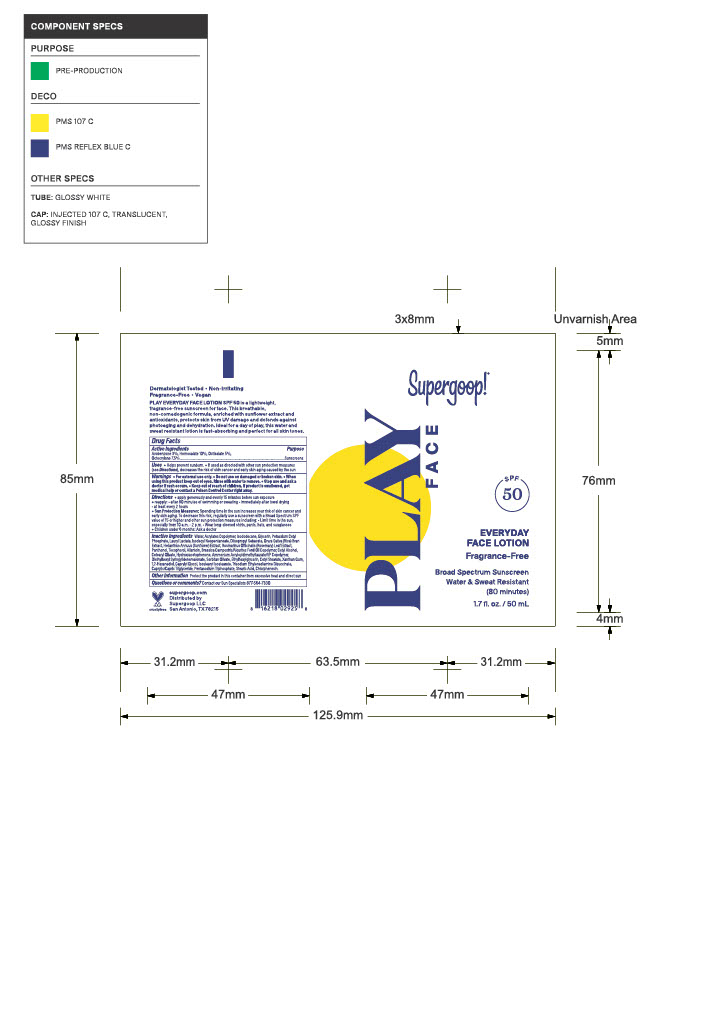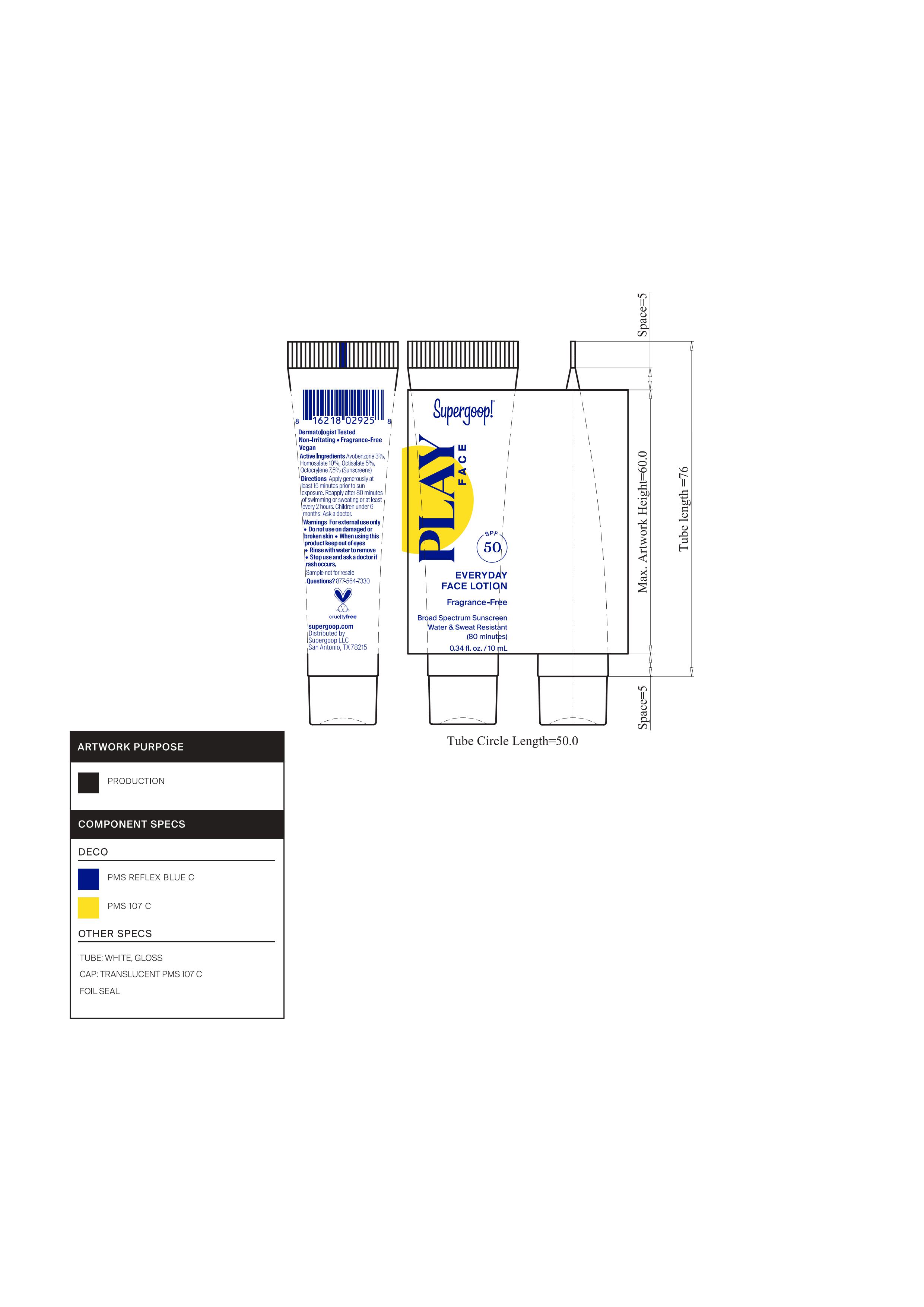 DRUG LABEL: Play Everyday Face SPF 50
NDC: 75936-653 | Form: LOTION
Manufacturer: Supergoop, LLC
Category: otc | Type: HUMAN OTC DRUG LABEL
Date: 20260121

ACTIVE INGREDIENTS: HOMOSALATE 10 g/100 mL; OCTISALATE 5 g/100 mL; OCTOCRYLENE 7.5 g/100 mL; AVOBENZONE 3 g/100 mL
INACTIVE INGREDIENTS: MEDIUM-CHAIN TRIGLYCERIDES; WATER; DIISOPROPYL SEBACATE; GLYCERIN; ISODECYL NEOPENTANOATE; ISODODECANE; LAURYL LACTATE; CETYL ALCOHOL; POTASSIUM CETYL PHOSPHATE; RICE BRAN; CETEARYL OLIVATE; AMMONIUM ACRYLOYLDIMETHYLTAURATE/VP COPOLYMER; HYDROXYACETOPHENONE; SORBITAN OLIVATE; DIETHYLHEXYL SYRINGYLIDENEMALONATE; CHLORPHENESIN; PENTYLENE GLYCOL; 1,2-HEXANEDIOL; CAPRYLYL GLYCOL; XANTHAN GUM; HELIANTHUS ANNUUS FLOWERING TOP; ISOSTEARYL ISOSTEARATE; TRISODIUM ETHYLENEDIAMINE DISUCCINATE; TOCOPHEROL; ALLANTOIN; ROSEMARY; PANTHENOL; SODIUM TRIPOLYPHOSPHATE ANHYDROUS; CITRIC ACID MONOHYDRATE; STEARIC ACID; ETHYLHEXYLGLYCERIN; TRIMETHYLOLPROPANE TRIACRYLATE; TERT-BUTYL ALCOHOL; 2-ACRYLAMIDO-2-METHYL-1-PROPANESULFONIC ACID; CETYL STEARATE; 1,5-PENTANEDIOL

Play Everyday Lotion SPF 50 With Sunflower Extract

Active Ingredients Purpose

Avobenzone 3% Sunscreen

Homosalate 10% Sunscreen

Octisalate 5% Sunscreen

Octocrylene 7.5% Sunscreen

Uses

Helps Prevent Sunburn

If used as directed with other sun protection measures (see Directions), decreases the risk of Skin cancer and early skin aging caused by the sun

Keep out of reach of children.

Stop use and ask a doctor if rash occurs

WARNINGS

For External use only

Do not use on damaged or broken skin

When using this product, Keep out of eyes. Rinse with water to remove

If swallowed, get medical help or contact a Poison Control Center right away

Directions

- Apply liberally 15 minutes before sun exposure

Reapply:

- after 80 minutes of swimming or sweating
- immediately after towel drying
- at least every 2 hours
- Sun Protection Measures. Spending time in the sun increases your risk of skin

cancer and early skin aging. To decrease this risk, regularly use a sunscreen
with broad spectrum SPF of 15 or higher and other sun protection measures
including:

- limit time in the sun, especially from 10 a.m. - 2 p.m.
- Wear Long-sleeved shirts, pants, hats, and sunglasses
- Children under 6 months: Ask a doctor

INACTIVE INGREDIENT

Water, Acrylates Copolymer, Isododecane, Glycerin, Potassium Cetyl Phosphate, Lauryl
Lactate, Isodecyl Neopentanoate, Diisopropyl Sebacate, Oryza Sativa (Rice) Bran Extract, Helianthus Annuus (Sunflower) Extract, Rosmarinus Officinalis (Rosemary) Leaf Extract, Panthenol, Tocopherol, Allantoin, Brassica Campestris/Aleurites Fordi Oil Copolymer, Cetyl Alcohol, Cetearyl Olivate, Hydroxyacetophenone, Ammonium Acryloyldimethyltaurate/VP Copolymer, Diethylhexyl Syringylidenemalonate, Sorbitan Olivate, Ethylhexylglycerin, Cetyl Stearate, Xanthan Gum, 1,2-Hexanediol, Caprylyl Glycol, Isostearyl Isostearate, Trisodium Ethylenediamine Disuccinate, Caprylic/Capric Triglyceride, Pentasodium Triphosphate, Stearic Acid, Chlorphenesin.

PACKAGE LABEL

PLAY Evergyday Face Lotion

SPF 50

Fragrance-Free

Broad Spectrum Sunscreen

Water and Sweat Resistant (80 minutes)